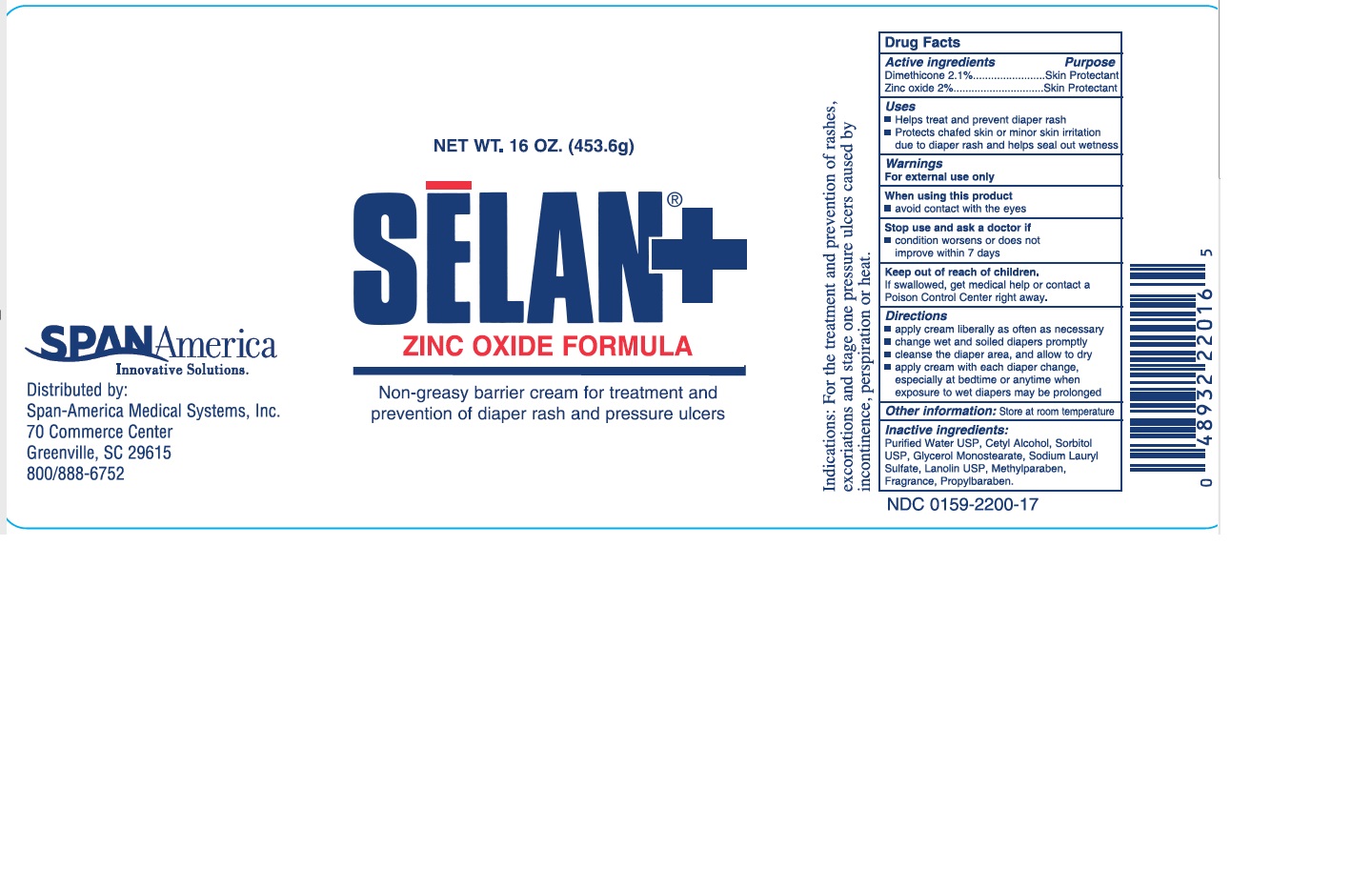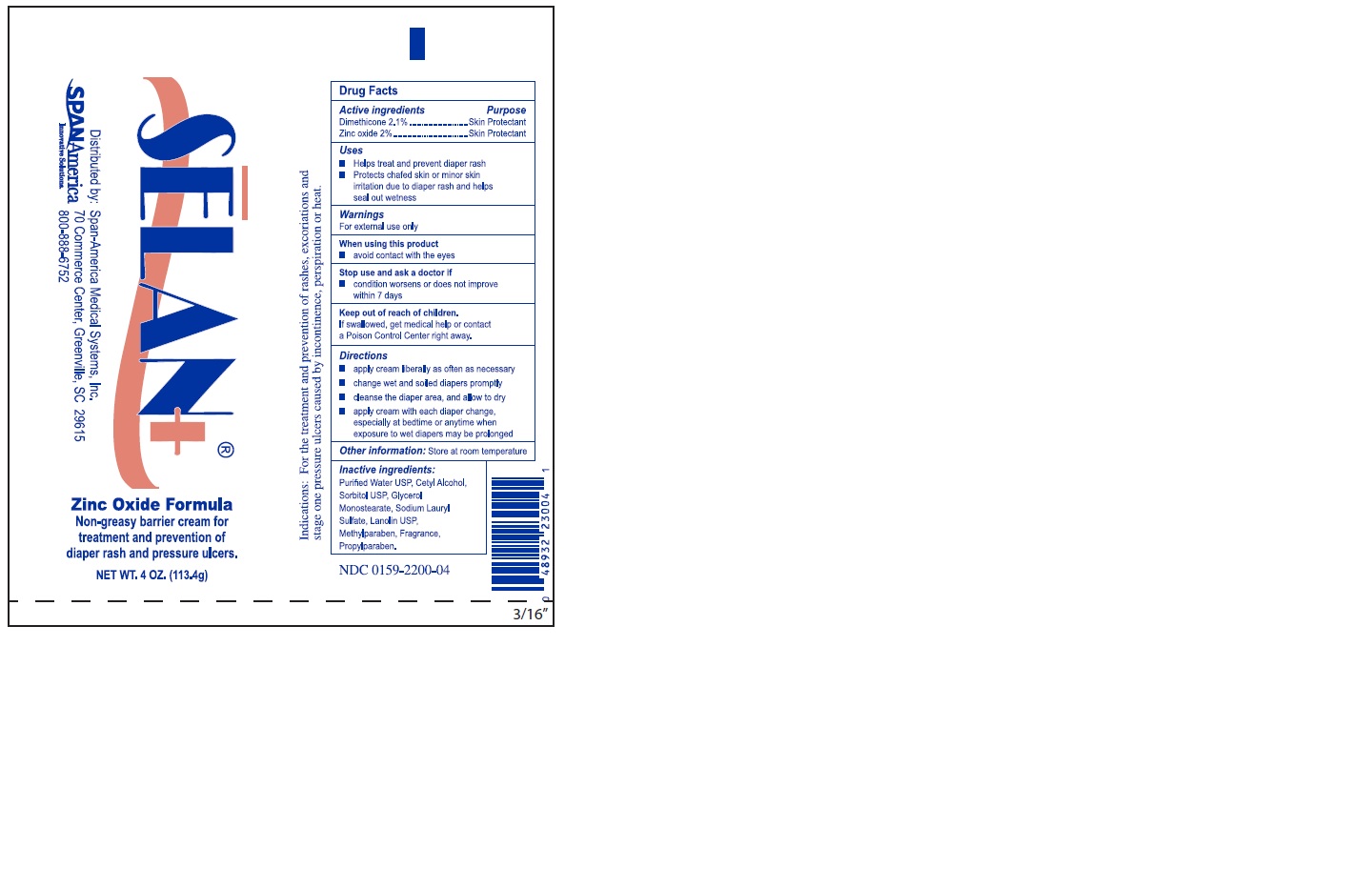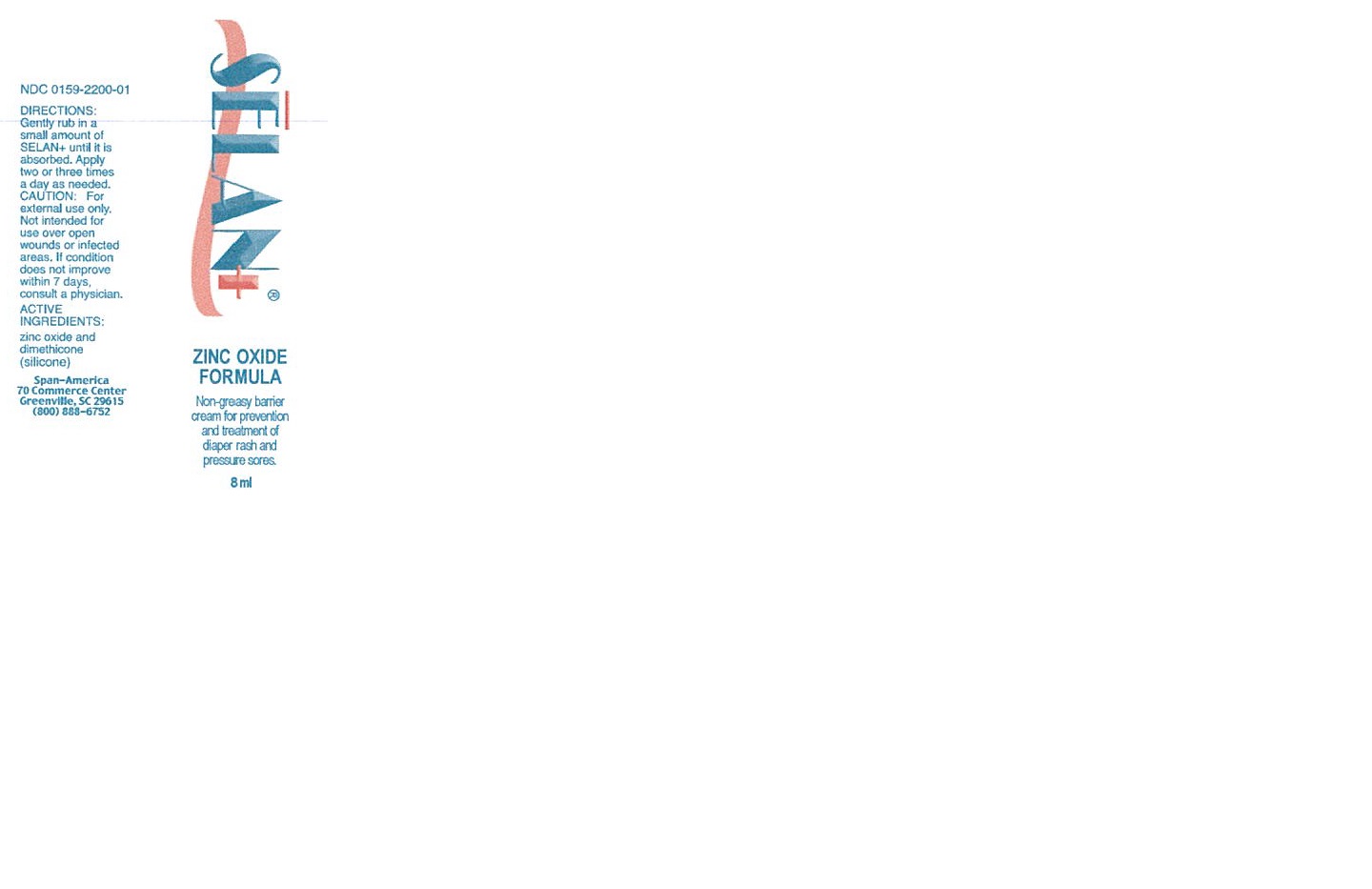 DRUG LABEL: Selan Plus Zinc Oxide
NDC: 0159-2200 | Form: CREAM
Manufacturer: Trividia Manufacturing Solutions, Inc
Category: otc | Type: HUMAN OTC DRUG LABEL
Date: 20251107

ACTIVE INGREDIENTS: ZINC OXIDE 2 g/100 g; DIMETHICONE 2.1 g/100 g
INACTIVE INGREDIENTS: WATER; CETYL ALCOHOL; GLYCERYL MONOSTEARATE; LANOLIN; SORBITOL; SODIUM LAURYL SULFATE; METHYLPARABEN; PROPYLPARABEN

Selan Plus Zinc Oxide

Active Ingredients

Dimethicone 2.1%

Zinc Oxide 2%

Purpose

Skin Protectant

Uses

- Helps treat and prevent diaper rash
- Protects chaged skin or minor skin irritation due to diaper rash and helps seal out wetness

Warnings

For external use only

When using this product

- avoid contact with the eyes

Stop use and ask a doctor if

- condition worsens or does not improve within 7 days

Keep out of reach of children.

If swallowed, get medical help or contact a Poison Control Center right away

Directions

- apply cream liberally as often as necessary
- change wet and soiled diapers promptly
- cleanse the diaper area, and allow to dry
- apply cream with each diaper change, especially at bedtime or anytime when exposure to wet diapers may be prolonged

Other Information:

Store at room temperature

INACTIVE INGREDIENT

Purified Water USP, Cetyl Alcohol, Sorbitol USP, Glycerol Monostearate, Sodium Lauryl Sulfate, Lanolin USP, Methylparaben, Fragrance, Propylparaben.